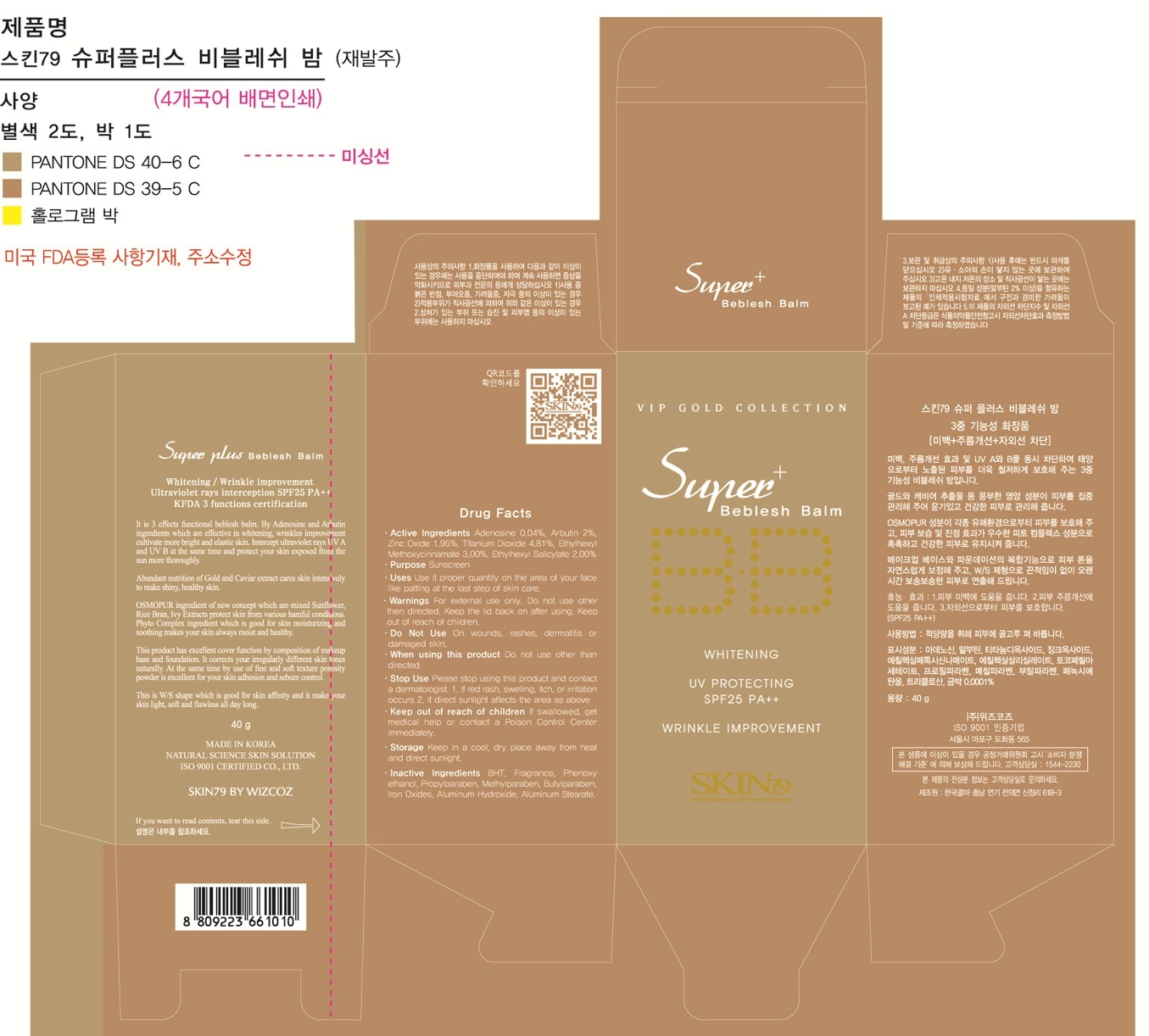 DRUG LABEL: SuperPlus Beblesh Balm SPF25 PA 2Plus
NDC: 49715-018 | Form: CREAM
Manufacturer: WIZCOZ CORPORATION LTD
Category: otc | Type: HUMAN OTC DRUG LABEL
Date: 20120201

ACTIVE INGREDIENTS: TITANIUM DIOXIDE 1.92 g/40 g; ZINC OXIDE 0.78 g/40 g; ARBUTIN 0.8 g/40 g; ADENOSINE 0.016 g/40 g; OCTINOXATE 1.2 g/40 g; OCTISALATE 0.8 g/40 g
INACTIVE INGREDIENTS: ALUMINUM HYDROXIDE; ALUMINUM STEARATE; BUTYLATED HYDROXYTOLUENE; BUTYLPARABEN; METHYLPARABEN; FERRIC OXIDE RED; PHENOXYETHANOL; PROPYLPARABEN

Purpose: Sunscreen

ACTIVE INGREDIENT

Active Ingredients: Titanium Dioxide 4.81%, Octinoxate 3.00%, Octisalate 2.00%, Arbutin 2.00%, Zinc Oxide 1.95%, Adenosine 0.04%

When using this product: Do not use other than directed

Do Not Use: On wounds, rashes, dermatitis or damaged skin

Keep Out of Reach of Children: If swallowed, get medical help or contact a Poison Control Center immediately

Stop Use: Please stop using this product and contact a dermatologist.
1. If red rash, swelling, itch or irritation occurs
2. If direct sunlight affects the area as above

WARNINGS

Warnings: For external use only. Do not use other than directed. Keep the lid back on after using

STORAGE AND HANDLING

Storage: Keep in a cool, dry place away from heat and direct sunlight

DESCRIPTION

Direction:
Step 1: Clean and dry your face
Step 2: Use the basic skincare products
Step 3: Use small amount of it and apply evenly and thoroughly to your face

INACTIVE INGREDIENT

Inactive Ingredients: Aluminum Hydroxide, Aluminum Stearate, BHT, Butylparaben, Methylparaben, Iron Oxide, Phenoxyethanol, Propylparaben